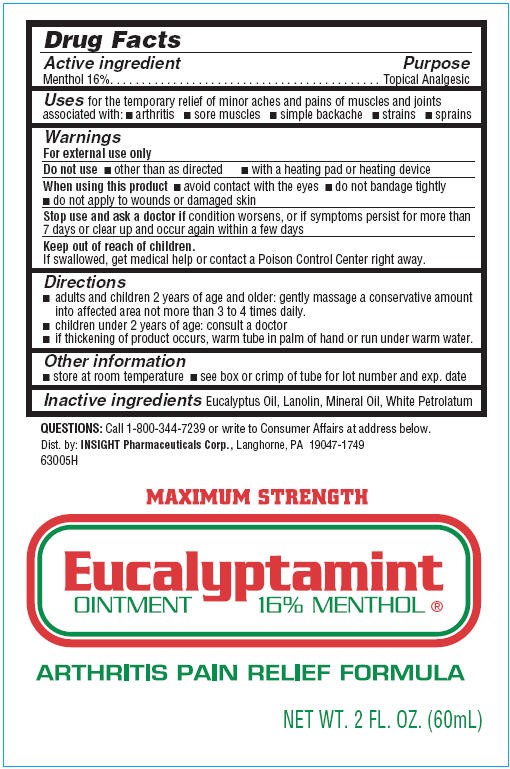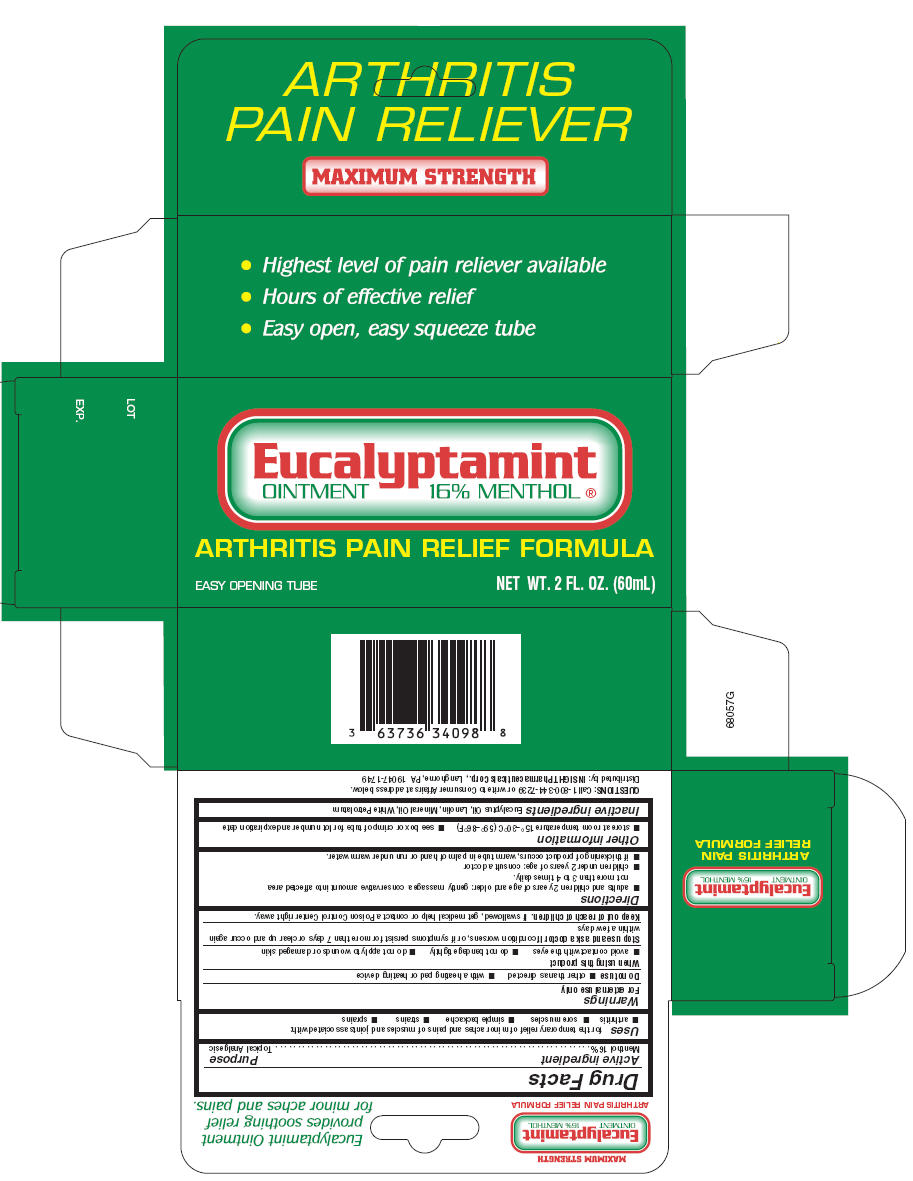 DRUG LABEL: Eucalyptamint
NDC: 63736-340 | Form: OINTMENT
Manufacturer: Insight Pharmaceuticals
Category: otc | Type: HUMAN OTC DRUG LABEL
Date: 20090720

ACTIVE INGREDIENTS: Menthol 9.6 mL/60 mL
INACTIVE INGREDIENTS: Eucalyptus Oil; Mineral Oil; Petrolatum

Eucalyptamint
OINTMENT 16% MENTHOL®

Drug Facts

Active ingredient

Menthol 16%

Purpose

Topical Analgesic

Uses

for the temporary relief of minor aches and pains of muscles and joints associated with:

- arthritis
- sore muscles
- simple backache
- strains
- sprains

Warnings

For external use only

Do not use

- other than as directed
- with a heating pad or heating device

When using this product

- avoid contact with the eyes
- do not bandage tightly
- do not apply to wounds or damaged skin

Stop use and ask a doctor if condition worsens, or if symptoms persist for more than 7 days or clear up and occur again within a few days

Keep out of reach of children.

If swallowed, get medical help or contact a Poison Control Center right away.

Directions

- adults and children 2 years of age and older: gently massage a conservative amount into affected area not more than 3 to 4 times daily.
- children under 2 years of age: consult a doctor
- if thickening of product occurs, warm tube in palm of hand or run under warm water.

Other information

- store at room temperature
- see box or crimp of tube for lot number and exp. date

Inactive ingredients

Eucalyptus Oil, Lanolin, Mineral Oil, White Petrolatum

QUESTIONS

Call 1-800-344-7239 or write to Consumer Affairs at address below.

Dist. by: INSIGHT Pharmaceuticals Corp., Langhorne, PA 19047-1749

63005H

PRINCIPAL DISPLAY PANEL - Tube Label

MAXIMUM STRENGTH

Eucalyptamint
OINTMENT 16% MENTHOL®

ARTHRITIS PAIN RELIEF FORMULA

NET WT. 2 FL. OZ. (60mL)

PRINCIPAL DISPLAY PANEL - Carton Label

Eucalyptamint
OINTMENT 16% MENTHOL®

ARTHRITIS PAIN RELIEF FORMULA

EASY OPENING TUBE
NET WT. 2 FL. OZ. (60mL)